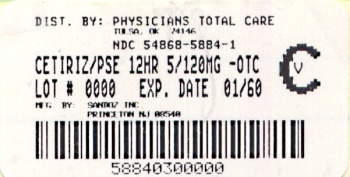 DRUG LABEL: Cetirizine HCl and Pseudoephedrine HCl
NDC: 54868-5884 | Form: TABLET, FILM COATED, EXTENDED RELEASE
Manufacturer: Physicians Total Care, Inc.
Category: otc | Type: HUMAN OTC DRUG LABEL
Date: 20100607
DEA Schedule: CV

ACTIVE INGREDIENTS: CETIRIZINE HYDROCHLORIDE 5 mg/1 1; PSEUDOEPHEDRINE HYDROCHLORIDE 120 mg/1 1
INACTIVE INGREDIENTS: SILICON DIOXIDE; CROSCARMELLOSE SODIUM; D&C YELLOW NO. 10; FERRIC OXIDE RED; FERRIC OXIDE YELLOW; HYPROMELLOSE 2208 (15000 CPS); LACTOSE MONOHYDRATE; MAGNESIUM STEARATE; CELLULOSE, MICROCRYSTALLINE; POLYETHYLENE GLYCOL; POLYSORBATE 80; POVIDONE; TITANIUM DIOXIDE

Drug Facts

Active Ingredient (in each extended release tablet)

Cetirizine HCl 5 mg

Pseudoephedrine HCl 120 mg

Purpose

Antihistamine

Nasal decongestant

Uses

- temporarily relieves these symptoms due to hay fever or other upper respiratory allergies:
  - runny nose
  - itchy, watery eyes
  - nasal congestion
  - sneezing
  - itching of the nose or throat
- reduces swelling of nasal passages
- temporarily relieves sinus congestion and pressure
- temporarily restores freer breathing through the nose

Warnings

Do not use

- if you have ever had an allergic reaction to this product or any of its ingredients or to an antihistamine containing hydroxyzine.
- if you are now taking a prescription monoamine oxidase inhibitor (MAOI) (certain drugs for depression, psychiatric, or emotional conditions, or Parkinson’s disease), or for 2 weeks after stopping the MAOI drug. If you do not know if your prescription drug contains an MAOI, ask a doctor or pharmacist before taking this product.

Ask a doctor before use if you have

- heart disease
- thyroid disease
- diabetes
- glaucoma
- high blood pressure
- trouble urinating due to an enlarged prostate gland
- liver or kidney disease.Your doctor should determine if you need a different dose.

Ask a doctor or pharmacist before use if you are

taking tranquilizers or sedatives.

When using this product

- do not use more than directed
- drowsiness may occur
- avoid alcoholic drinks
- alcohol, sedatives, and tranquilizers may increase drowsiness
- be careful when driving a motor vehicle or operating machinery

Stop use and ask a doctor if

- an allergic reaction to this product occurs. Seek medical help right away.
- you get nervous, dizzy, or sleepless
- symptoms do not improve within 7 days or are accompanied by fever

If pregnant or breast-feeding:

- If breast-feeding: not recommended
- If pregnant: ask a health professional before use.

Keep out of reach of children.

In case of overdose, get medical help or contact a Poison Control Center right away.

Directions

- do not break or chew tablet; swallow tablet whole

adults and children 12 years and over | take 1 tablet every 12 hours; do not take more than 2 tablets in 24 hours.
adults 65 years and over | ask a doctor
children under 12 years of age | ask a doctor
consumers with liver or kidney disease | ask a doctor

Other Information

- Safety sealed: do not use if the imprinted bottle seal is open or torn (for bottle only).
- DO NOT USE IF BLISTER UNIT IS BROKEN OR TORN (for blister package only).

STORAGE AND HANDLING

Store at 20°-25°C (68°-77°F) (see USP Controlled Room Temperature).

Inactive Ingredients

Colloidal silicon dioxide, croscarmellose sodium, D & C yellow aluminum lake, hypromellose, iron oxide red, iron oxide yellow, lactose monohydrate, magnesium stearate, microcrystalline cellulose, polyethylene glycol, polysorbate, povidone, and titanium dioxide.

Questions or comments?

1-800-525-8747

Sandoz Inc.

Princeton, NJ 08540

05-2010M

Relabeling of Additional Barcode by:
Physicians Total Care, Inc.
Tulsa, OK 74146

HOW SUPPLIED:

30 Tablets, Bottles NDC 54868-5884-1

60 Tablets, Bottles NDC 54868-5884-0

24 Tablets, Blister Pack NDC 54868-5884-2

5 mg/120 mg Label

Cetirizine HCl and

Pseudoephedrine HCl

Extended Release Tablets

5 mg/120 mg

antihistamine/

nasal decongestant

Indoor & Outdoor Allergies

ALLERGY & CONGESTION

12 hour Relief of

Runny Nose Itchy, Watery Eyes Sinus Pressure

Sneezing Itchy Throat or Nose Nasal Congestion